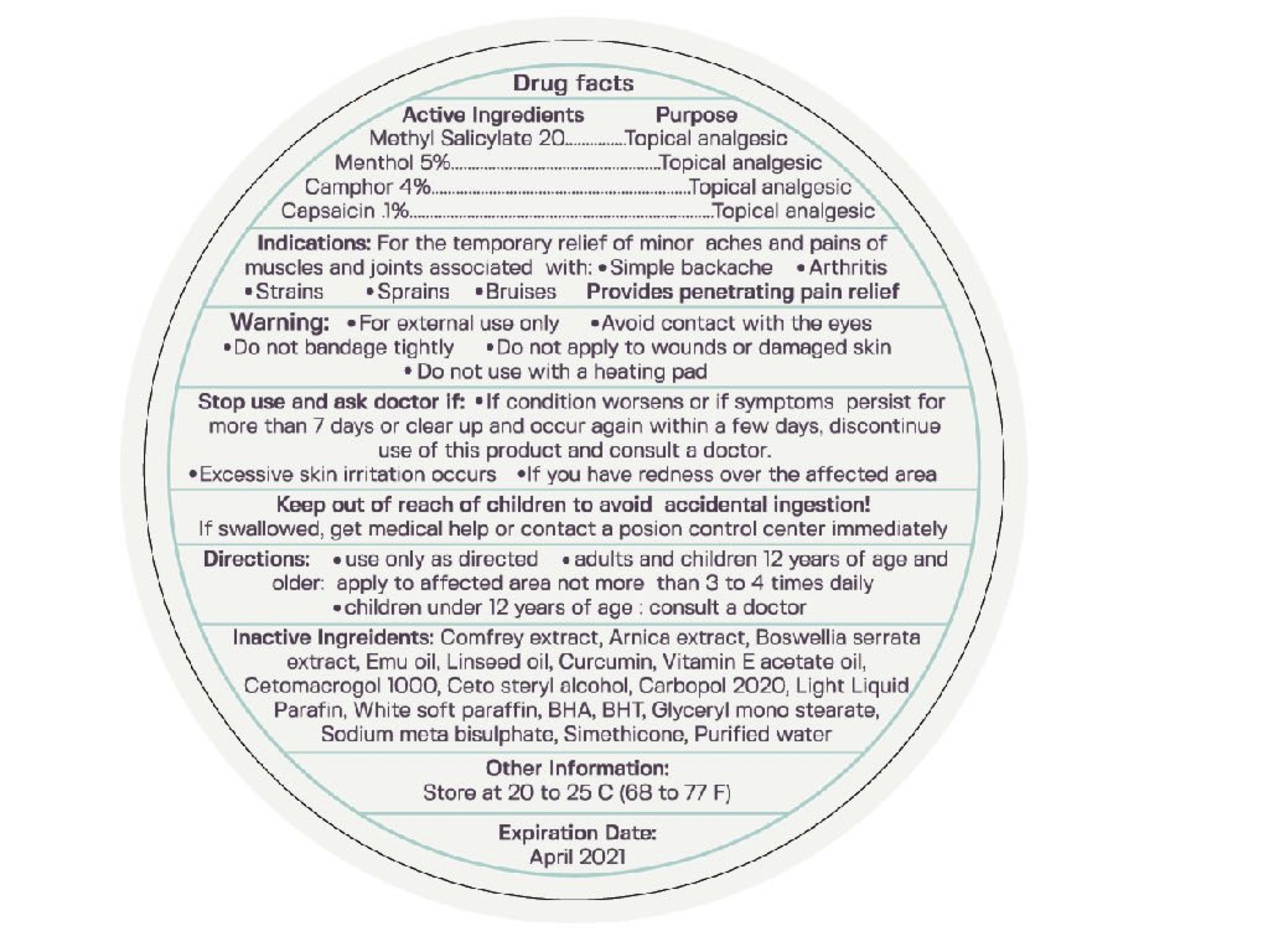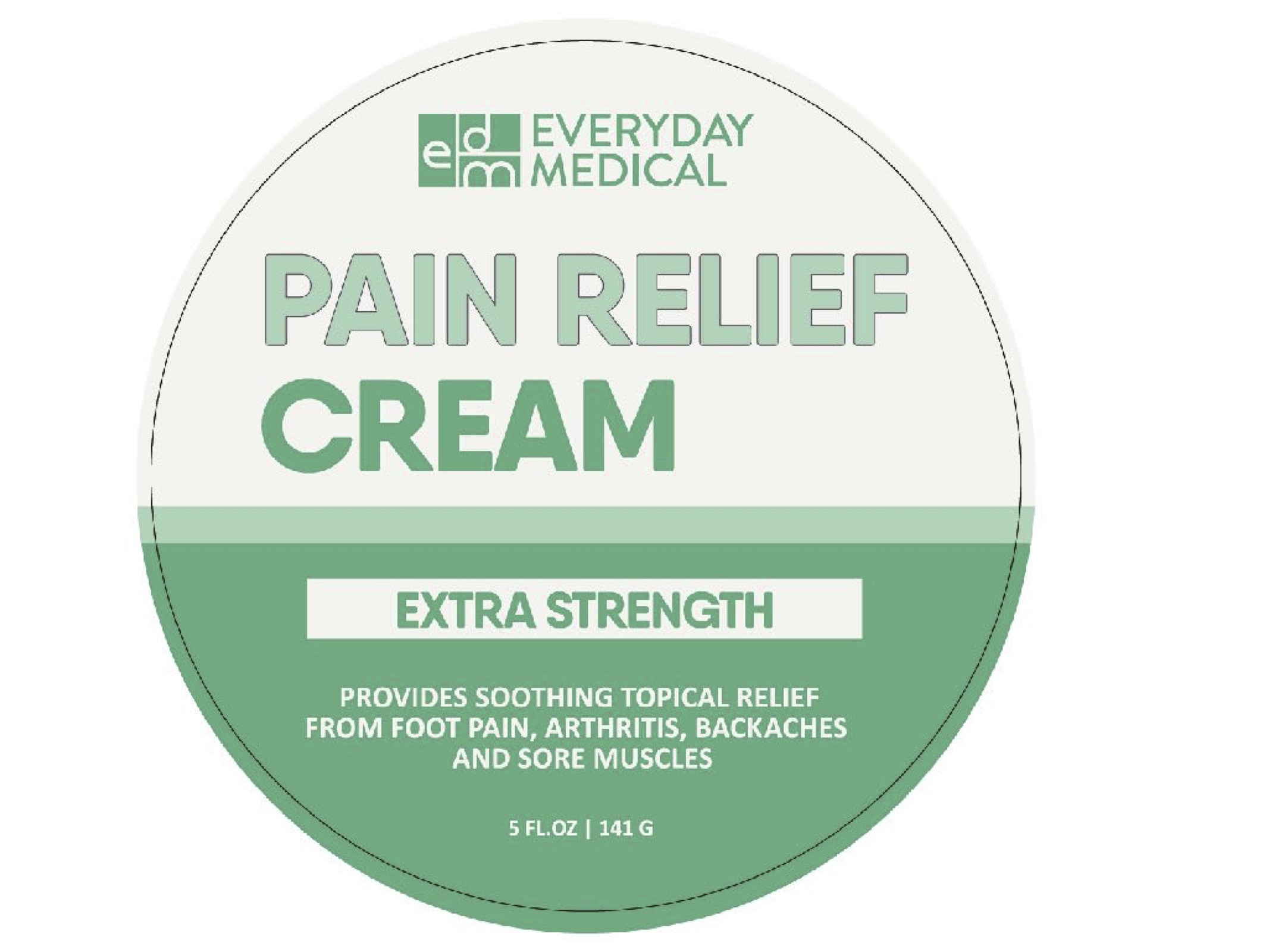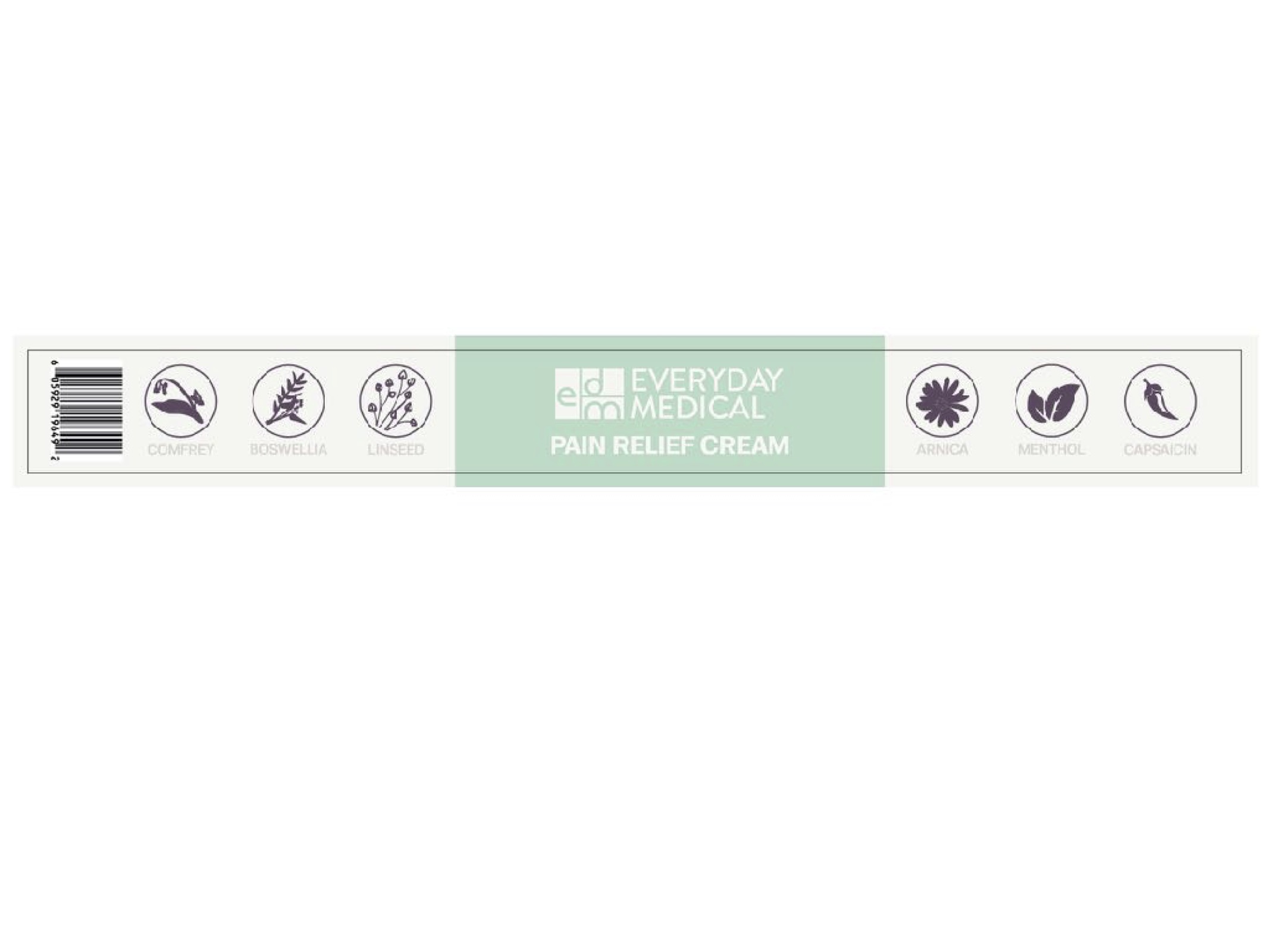 DRUG LABEL: Pain Relief Cream Extra Strength
NDC: 72982-1901 | Form: CREAM
Manufacturer: Everyday Medical LLC
Category: otc | Type: HUMAN OTC DRUG LABEL
Date: 20200113

ACTIVE INGREDIENTS: MENTHOL 5 g/100 g; CAMPHOR (NATURAL) 4 g/100 g; METHYL SALICYLATE 20 g/100 g; CAPSAICIN 0.01 g/100 g
INACTIVE INGREDIENTS: LINSEED OIL; WATER; CURCUMIN; ARNICA MONTANA; BOSWELLIA SERRATA WHOLE; ALPHA-TOCOPHEROL ACETATE; CETETH-20; CETOSTEARYL ALCOHOL; STEARIC ACID; COMFREY; EMU OIL

Pain Relief Cream Extra Strength

Active Ingredients Purpose

Methyl Salicylate 20% Topical Analgesic

Menthol 5% Topical Analgesic

Camphor 4% Topical Analgesic

Capsaicin.1% Topical Analgesic

PURPOSE

Topical analgesic

INDICATIONS AND USAGE

temporarily relieves minor pain associated with

- arthritis
- simple backache
- muscle strains
- bruises
- sprains
- cramps

Warnings

For external use only

When using this product: Use only as directed

- do not bandage tightly or use with a heating pad
- avoid contact with eyes and mucous membranes
- do not apply to wounds or damaged, broken or irritated skin
- if severe burning sensation occurs, discontinue use immediately

Stop use and ask a doctor if

- condition worsens
- redness is present
- irritation develops

Keep out of reach of children. If swallowed get medical help or contact a Poison Control Center right away

DOSAGE AND ADMINISTRATION

- Use only as directed
- Adults and children 12 years of age and older apply to affected area not more than 3 to 4 times daily
- Children under the age of 12 years of age consult a doctor

INACTIVE INGREDIENT

- Comfrey extract
- Arnica extract
- Boswellia serrata extract
- Emu oil
- Linseed oil
- Curcumin
- Vitamin E acetate oil
- Cetomacrogol 1000
- Ceto steryl alcohol
- Carbopol 2020
- Light liquid parafin
- White soft paraffin
- BHA
- BHT
- Glyceryl mono stearate
- Sodium meta bisulphate
- Simethicone
- Purified water